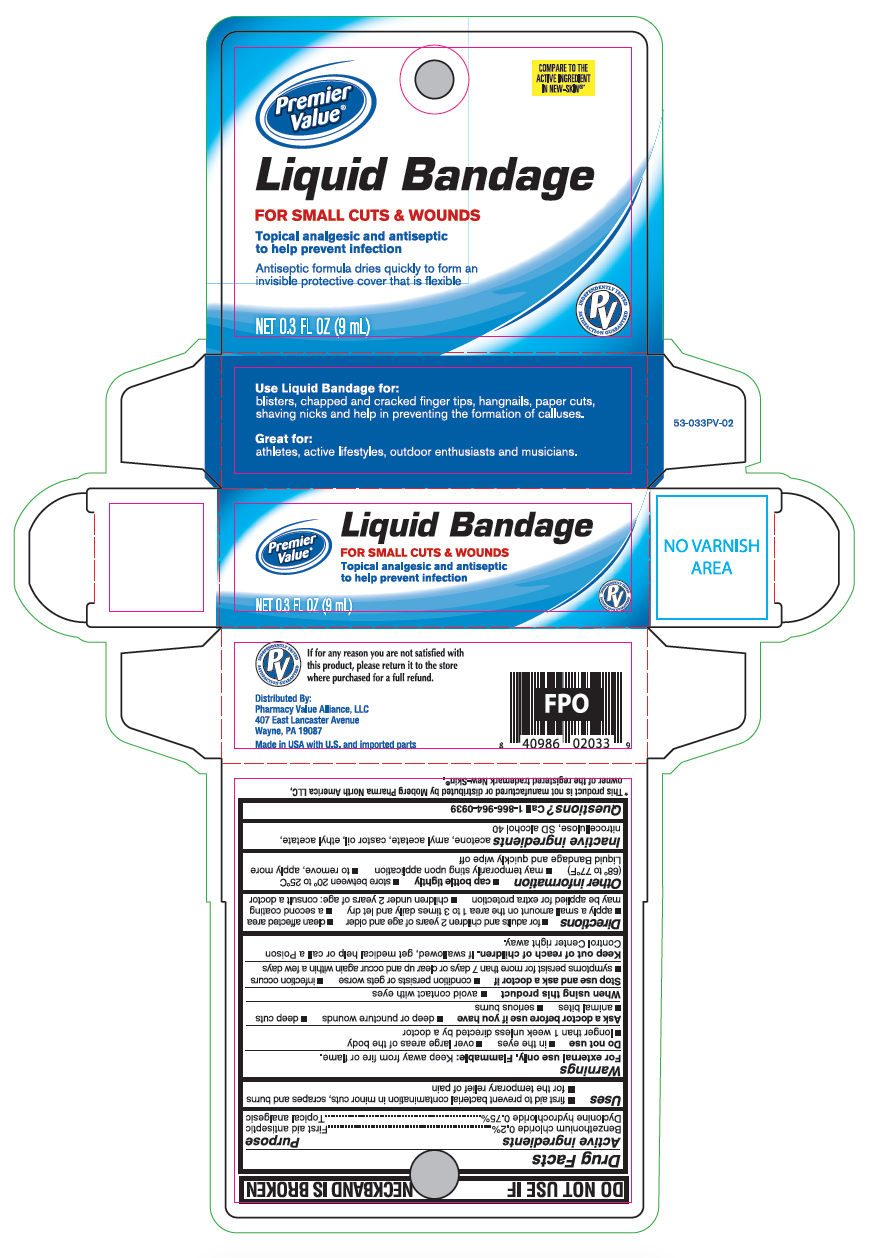 DRUG LABEL: Benzethonium chloride Plus Dyclonine hydrochloride
NDC: 68016-615 | Form: LIQUID
Manufacturer: Chain Drug Consortium, LLC
Category: otc | Type: HUMAN OTC DRUG LABEL
Date: 20260212

ACTIVE INGREDIENTS: BENZETHONIUM CHLORIDE 0.2 mg/9 mL; DYCLONINE HYDROCHLORIDE 0.75 mg/9 mL
INACTIVE INGREDIENTS: ACETONE; AMYL ACETATE; CASTOR OIL; ETHYL ACETATE; PYROXYLIN; ALCOHOL

Premier Value Liquid Bandage

Active ingredients

Benzethonium chloride 0.2%

Dyclonine hydrochloride 0.75%

Purpose

First aid antiseptic

Topical analgesic

Uses

- first aid to prevent bacterial contamination in minor cuts, scrapes and burns
- for the temporary relief of pain

Warnings

For external use only. Flammable: Keep away from fire or flame.

Do not use

- in the eyes
- overlarge areas of the body
- longer than 1 week unless directed by a doctor

Ask a doctor before use if you have

- deep puncture wounds
- deep cuts
- animal bites
- serious burns

When using this product

- avoid contact with eyes

Stop use and ask a doctor if

- conditions persists or gets worse
- infection occurs
- symptoms persists for more than 7 days or clear up and occur again within a few days

Keep out of reach of children.

If swallowed, get medical help or call a Poison Control Center right away.

Directions

- for adults and children 2 years of age and older
- clean affected area
- apply a small amount on the area 1 to 3 times daily and let dry
- a second coating may be applied for extra protection
- children under 2 years of age; consult a doctor

Other information

- cap bottle tightly
- store between 20° to 25°C (68° to 77°F)
- may temporarily sting upon application
- to remove, apply more Liquid Bandage and quickly wipe off

Inactive ingredients

acetone, amyl acetate, castor oil, ethyl acetate, nitrocellulose, SD slcohol 40

Questions

Call 1-866-964-0939

Principal Display Panel

Premier Value

Liquid Bandage

FOR SMALL CUTS & WOUNDS

Topical analgesic and antiseptic to help prevent infection

Antiseptic formula dries quickly to form an invisible protective cover that is flexible

0.3 FL OZ (9mL)

Use Liquid Bandage for:

blisters, chapped and cracked finger tips, hangnails, paper cuts, shaving nicks and help in preventing the formation of calluses.

Great for:

athletes, active lifestyles, outdoor enthusiasts and musicians.